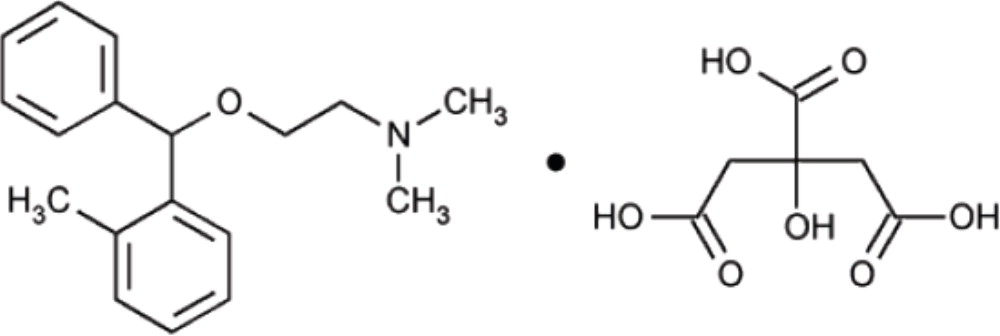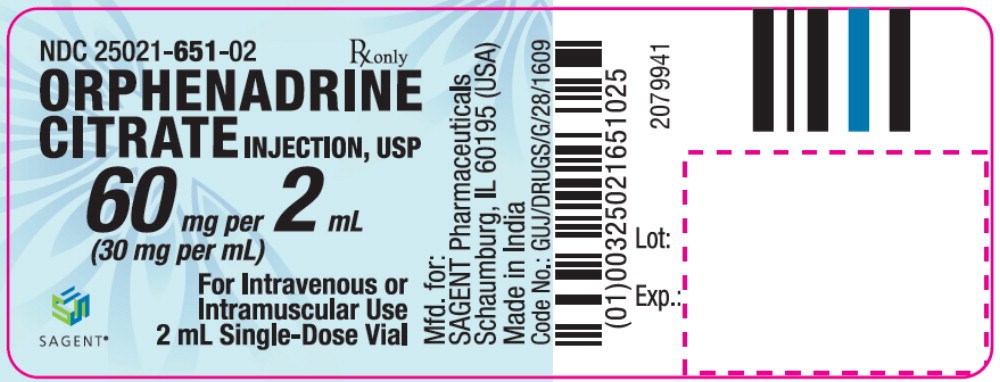 DRUG LABEL: Orphenadrine Citrate
NDC: 25021-651 | Form: INJECTION, SOLUTION
Manufacturer: Sagent Pharmaceuticals
Category: prescription | Type: HUMAN PRESCRIPTION DRUG LABEL
Date: 20231114

ACTIVE INGREDIENTS: orphenadrine citrate 30 mg/1 mL
INACTIVE INGREDIENTS: sodium metabisulfite 1 mg/1 mL; sodium chloride 2.9 mg/1 mL; sodium hydroxide; water

Orphenadrine Citrate Injection, USP
(For Intravenous or Intramuscular Use)

SAGENT®

Rx only

DESCRIPTION

Orphenadrine citrate is the citrate salt of orphenadrine (2-dimethylaminoethyl 2- methylbenzhydryl ether citrate). It occurs as a white, crystalline powder having a bitter taste. It is practically odorless; sparingly soluble in water, slightly soluble in alcohol.
It has the following structural formula:

The empirical formula is C18H23NO·C6H8O7, representing a molecular weight of 461.50.

Orphenadrine Citrate Injection, USP contains 60 mg of orphenadrine citrate in aqueous solution in each vial. Orphenadrine Citrate Injection, USP also contains: sodium metabisulfite NF, 2.0 mg; sodium chloride USP, 5.8 mg; sodium hydroxide NF, to adjust pH; and water for injection USP, q.s. to 2 mL.

CLINICAL PHARMACOLOGY

The mode of therapeutic action has not been clearly identified, but may be related to its analgesic properties. Orphenadrine citrate does not directly relax tense muscles in man. Orphenadrine citrate also possesses anti-cholinergic actions.

INDICATIONS AND USAGE

Orphenadrine Citrate Injection is indicated as an adjunct to rest, physical therapy, and other measures for the relief of discomfort associated with acute painful musculo skeletal conditions.

CONTRAINDICATIONS

Contraindicated in patients with glaucoma, pyloric or duodenal obstruction, stenosing peptic ulcers, prostatic hypertrophy or obstruction of the bladder neck, cardio-spasm (megaesophagus) and myasthenia gravis.

Contraindicated in patients who have demonstrated a previous hypersensitivity to the drug.

WARNINGS

Some patients may experience transient episodes of light-headedness, dizziness or syncope. Orphenadrine citrate may impair the ability of the patient to engage in potentially hazardous activities such as operating machinery or driving a motor vehicle; ambulatory patients should therefore be cautioned accordingly.

Orphenadrine citrate contains sodium metabisulfite, a sulfite that may cause allergic-type reactions including anaphylactic symptoms and life-threatening or less severe asthmatic episodes in certain susceptible people. The overall prevalence of sulfite sensitivity in the general population is unknown and probably low. Sulfite sensitivity is seen more frequently in asthmatic than nonasthmatic people.

PRECAUTIONS

Confusion, anxiety and tremors have been reported in few patients receiving propoxyphene and orphenadrine concomitantly. As these symptoms may be simply due to an additive effect, reduction of dosage and/or discontinuation of one or both agents is recommended in such cases.

Orphenadrine citrate should be used with caution in patients with tachycardia, cardiac decompensation, coronary insufficiency, cardiac arrhythmias.

Safety of continuous long-term therapy with orphenadrine has not been established. Therefore, if orphenadrine is prescribed for prolonged use, periodic monitoring of blood, urine and liver function values is recommended.

Pregnancy

Pregnancy Category C. Animal reproduction studies have not been conducted with orphenadrine citrate It is also not known whether orphenadrine citrate can cause fetal harm when administered to a pregnant woman or can affect reproduction capacity. Orphenadrine citrate should be given to a pregnant woman only if clearly needed.

Pediatric Use

Safety and effectiveness in pediatric patients have not been established.

ADVERSE REACTIONS

Adverse reactions of orphenadrine are mainly due to the mild anti-cholinergic action of orphenadrine, and are usually associated with higher dosage. Dryness of the mouth is usually the first adverse effect to appear. When the daily dose is increased, possible adverse effects include: tachycardia, palpitation, urinary hesitancy or retention, blurred vision, dilatation of pupils, increased ocular tension, weakness, nausea, vomiting, headache, dizziness, constipation, drowsiness, hypersensitivity reactions, pruritus, hallucinations, agitation, tremor, gastric irritation, and rarely urticaria and other dermatoses. Infrequently, an elderly patient may experience some degree of mental confusion. These adverse reactions can usually be eliminated by reduction in dosage. Very rare cases of aplastic anemia associated with the use of orphenadrine tablets have been reported. No causal relationship has been established.

Rare instances of anaphylactic reaction have been reported associated with the intramuscular injection of orphenadrine citrate.

To report SUSPECTED ADVERSE REACTIONS, contact Sagent Pharmaceuticals, Inc. at 1-866-625-1618 or FDA at 1-800-FDA-1088 or www.fda.gov/medwatch.

DRUG ABUSE AND DEPENDENCE

Orphenadrine has been chronically abused for its euphoric effects. The mood elevating effects may occur at therapeutic doses of orphenadrine.

OVERDOSAGE

Orphenadrine is toxic when overdosed and typically induces anticholinergic effects. In a review of orphenadrine toxicity, the minimum lethal dose was found to be 2 to 3 grams for adults; however, the range of toxicity is variable and unpredictable. Treatment for orphenadrine overdose is evacuation of stomach contents (when necessary), charcoal at repeated doses, intensive monitoring, and appropriate supportive treatment of any emergent anticholinergic effects.

DOSAGE AND ADMINISTRATION

INJECTION: Adults – One 2 mL vial (60 mg) intravenously or intramuscularly; may be repeated every 12 hours.

HOW SUPPLIED

Orphenadrine Citrate Injection, USP is supplied as follows:

NDC | Orphenadrine Citrate Injection, USP (30 mg per mL) | Package Factor
25021-651-02 | 60 mg per 2 mL Single-Dose Vial | 10 vials per carton

Orphenadrine Citrate Injection, USP is an aqueous solution.

Storage Conditions

Store at 20° to 25°C (68° to 77°F); excursions permitted between 15° and 30°C (59° and 86°F). [See USP Controlled Room Temperature.]

Protect from light. Retain in carton until time of use.

Not to be sold in unbroken box.

Discard unused portion.

Sterile, Nonpyrogenic, Preservative-free.
The container closure is not made with natural rubber latex.

SAGENT®

Mfd. for SAGENT Pharmaceuticals
Schaumburg, IL 60195 (USA)
Made in India
©2021 Sagent Pharmaceuticals, Inc.

Revised: May 2021

SAGENT Pharmaceuticals®

PACKAGE LABEL – PRINCIPAL DISPLAY PANEL – Vial Label

NDC 25021-651-02

Rx only

Orphenadrine Citrate Injection, USP

60 mg per 2 mL

(30 mg per mL)

For Intravenous or Intramuscular Use

2 mL Single-Dose Vial